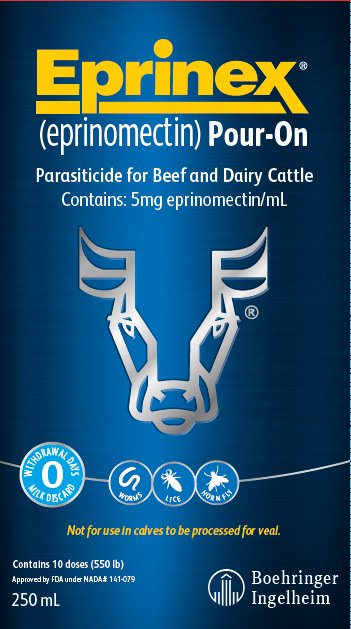 DRUG LABEL: EPRINEX
NDC: 0010-4751 | Form: SOLUTION
Manufacturer: Boehringer Ingelheim Animal Health USA Inc.
Category: animal | Type: OTC ANIMAL DRUG LABEL
Date: 20250423

ACTIVE INGREDIENTS: eprinomectin 5 mg/1 mL

Eprinex®
(eprinomectin) Pour-On

Approved by FDA under NADA # 141-079

Parasiticide for Beef and Dairy Cattle

Contains: 5 mg eprinomectin/mL

Not for use in calves to be processed for veal.

INTRODUCTION

EPRINEX Pour-On delivers effective internal and external parasite control in one application. Discovered and developed by scientists from Merck Research Laboratories, EPRINEX Pour-On contains eprinomectin, a unique avermectin. Its broad-spectrum efficacy in a weatherproof formulation, margin of safety, zero slaughter withdrawal and zero milk discard, make it a convenient product for parasite control in beef and dairy cattle, including lactating dairy cattle.

MODE OF ACTION

Eprinomectin is a member of the macrocyclic lactone class of endectocides which have a unique mode of action. Compounds of the class bind selectively and with high affinity to glutamate-gated chloride ion channels which occur in invertebrate nerve and muscle cells.

This leads to an increase in the permeability of the cell membrane to chloride ions with hyperpolarization of the nerve or muscle cell, resulting in paralysis and death of the parasite. Compounds of this class may also interact with other ligand-gated chloride channels, such as those gated by the neurotransmitter gamma-aminobutyric acid (GABA).

The margin of safety for compounds of this class is attributable to the fact that mammals do not have glutamate-gated chloride channels, the macrocyclic lactones have a low affinity for other mammalian ligand-gated chloride channels and they do not readily cross the blood-brain barrier.

INDICATIONS

EPRINEX (eprinomectin) Pour-On is indicated for the treatment and control of gastrointestinal roundworms (including inhibited Ostertagia ostertagi), lungworms, grubs, sucking and biting lice, chorioptic and sarcoptic mange mites, and horn flies in beef and dairy cattle of all ages, including lactating dairy cattle.

Applied at the recommended dose volume of 1 mL/10 kg (22 lb) body weight, to achieve a dose level of 500 mcg eprinomectin/kg body weight, EPRINEX Pour-On is indicated for the effective treatment and control of the following parasites.

Gastrointestinal Roundworms
Haemonchus placei | (adults and L4)
Ostertagia ostertagi (including inhibited L4) | (adults and L4)
Trichostrongylus axei | (adults and L4)
Trichostrongylus colubriformis | (adults and L4)
Trichostrongylus longispicularis | (adults only)
Cooperia oncophora | (adults and L4)
Cooperia punctata | (adults and L4)
Cooperia surnabada | (adults and L4)
Nematodirus helvetianus | (adults and L4)
Oesophagostomum radiatum | (adults and L4)
Bunostomum phlebotomum | (adults and L4)
Strongyloides papillosus | (adults only)
Trichuris spp. | (adults only)
Lungworms
Dictyocaulus viviparus | (adults and L4)
Cattle Grubs (all parasitic stages)
Hypoderma lineatum, Hypoderma bovis
Lice
Damalinia bovis, Linognathus vituli, Haematopinus
eurysternus, Solenopotes capillatus
Mange Mites
Chorioptes bovis, Sarcoptes scabiei
Horn Flies
Haematobia irritans

Persistent Activity

EPRINEX (eprinomectin) Pour-On for Beef and Dairy Cattle has been proved to effectively control infections and to protect cattle from re-infection with Dictyocaulus viviparus for 21 days after treatment and Haematobia irritans for 7 days after treatment.

Use Conditions

Varying weather conditions, including rainfall, do not affect the efficacy of EPRINEX Pour-On.

Management Considerations for Treatment of External Parasites

For best results EPRINEX Pour-On should be applied to all cattle in the herd. Cattle introduced to the herd later should be treated prior to introduction. Consult your veterinarian or an entomologist for the most effective timing of applications for the control of external parasites.

Chorioptic Mange: In clinical studies evaluating the efficacy of EPRINEX Pour-On against chorioptic mange mites, mites were not recovered from skin scrapings taken 8 weeks after treatment; however, chronic skin lesions were still present on some animals.

Horn flies: For optimal control of horn flies, as EPRINEX Pour-On provides 7 days of persistent activity against horn flies, the product should be used as part of an integrated control program utilizing other control methods to provide extended control.

DOSAGE

The product is formulated only for external application to beef and dairy cattle. The dose rate is 1 mL/10 kg (22 lb) of body weight. The product should be applied topically along the backline in a narrow strip extending from the withers to the tailhead.

Do not underdose. Ensure each animal receives a complete dose based on a current body weight. Underdosing may result in ineffective treatment, and encourage the development of parasite resistance.

ADMINISTRATION

Metering Cup with Measure-Squeeze-Pour System

250 mL Container with 25 mL Metering Cup

1 Liter Container with 60 mL Metering Cup

This pack contains 1 Metering Cup and 1 dip tube

1. Insert the dip tube into base of the Metering Cup. Leave the "slotted end" of the dip tube exposed in the bottom of the container.
2. Unscrew shipping cap from container top.
3. Screw the Metering Cup onto container top.
4. Measure: To select the correct dose rate, rotate the adjuster cap (top) in either direction to position the dose indicator to the weight of the animal you want to treat. When body weight is between markings, use the higher setting.
5. Squeeze the container gently to fill the Metering Cup to the required dose. Release your grip and any excess will return to the container.
6. Pour: Apply the full dose by tipping and pouring along the backline of the animal until the Metering Cup is empty.
7. Storage: The Metering Cup should not remain attached to the container when not in use. Detach the Metering Cup after each use and replace the shipping cap to close the container top.

Collapsible Pack (2.5 L, 5 L, and 10 L Packs)

Connect the dosing applicator and draw-off tubing to the collapsible pack as follows:

Attach the open end of the draw-off tubing to an appropriate dosing applicator. Attach draw-off tubing to the cap with the stem that is included in the pack (10 L contains two caps – one for inverted use and the other for upright use). Replace the shipping cap with the cap having the draw-off tubing.

Gently prime the dosing applicator, checking for leaks. Follow the dosing applicator manufacturer's directions for adjusting the dose and proper use and maintenance of the dosing applicator and draw-off tubing.

20 Liter Pack (20 L Pack)

Connect the dosing applicator and draw-off tubing to the container as follows:

Attach the open end of the draw-off tubing to an appropriate dosing applicator. Attach draw-off tubing to the cap with the stem. Replace the shipping cap with the cap having the draw-off tubing.

Gently prime the dosing applicator, checking for leaks. Follow the dosing applicator manufacturer's directions for adjusting the dose and proper use and maintenance of the dosing applicator and draw-off tubing.

ANIMAL SAFETY

Tolerance and toxicity studies have demonstrated the margin of safety for eprinomectin in cattle. In toxicity studies, application of 3 times the recommended dose had no adverse effects on neonatal calves, and application of up to 5 times the recommended dose 3 times at 7 day intervals had no adverse effects on 8 week old calves. In the tolerance study, one of 6 cattle treated once at 10 times the recommended dose showed clinical signs of mydriasis. Application of 3 times the recommended dose had no adverse effect on breeding performance of cows or bulls.

RESIDUE WARNING

Residue Warnings: When used according to label directions, neither a pre-slaughter drug withdrawal period nor a milk discard time is required, therefore, meat and milk from cattle treated with EPRINEX (eprinomectin) Pour-On may be used for human consumption at any time following treatment. A withdrawal period has not been established for pre-ruminating calves. Do not use in calves to be processed for veal.

WARNING:

Keep this and all drugs out of the reach of children.

NOT FOR USE IN HUMANS.

As with any topical medication intended for treatment of animals, skin contact should be avoided. If accidental skin contact occurs, wash immediately with soap and water. If accidental eye exposure occurs, flush eyes immediately with water. The Safety Data Sheet (SDS) contains more detailed occupational safety information.

To report suspected adverse drug events, for technical assistance, or to obtain a copy of the SDS, contact Boehringer Ingelheim Animal Health USA Inc. at 1-888-637-4251. For additional information about adverse drug experience reporting for animal drugs, contact FDA at 1-888-FDA-VETS, or online at www.fda.gov/reportanimalae.

PRECAUTIONS

This product is for topical application only. Do not administer orally or by injection.

Do not apply to areas of the backline covered with mud or manure.

EPRINEX Pour-On is not recommended for use in species other than cattle. Severe adverse reactions have been reported in other species treated with products containing compounds of this class.

Restricted Drug (California) - Use only as directed.

When to Treat Cattle with Grubs

EPRINEX Pour-On is effective against all stages of cattle grubs. However, proper timing of treatment is important. For the most effective results, cattle should be treated as soon as possible after the end of the heel fly (warble fly) season. While this is not peculiar to eprinomectin, destruction of Hypoderma larvae (cattle grubs) at the period when these grubs are in vital areas may cause undesirable host-parasite reactions. Killing Hypoderma lineatum when it is in the esophageal tissues may cause bloat; killing H. bovis when it is in the vertebral canal may cause staggering or paralysis. Cattle should be treated either before or after these stages of grub development.

Cattle treated with EPRINEX Pour-On at the end of the fly season may be re-treated with EPRINEX Pour-On during the winter without danger of grub-related reactions. For further information and advice on a planned parasite control program, consult your veterinarian.

OTHER WARNINGS

Parasite resistance may develop to any dewormer, and has been reported for most classes of dewormers.

Treatment with a dewormer used in conjunction with parasite management practices appropriate to the

geographic area and the animal(s) to be treated may slow the development of parasite resistance.

Fecal examinations or other diagnostic tests and parasite management history should be used to determine if the product is appropriate for the herd prior to the use of any dewormer. Following the use of any dewormer, effectiveness of treatment should be monitored (for example, with the use of a fecal egg count reduction test or another appropriate method).

A decrease in a drug’s effectiveness over time as calculated by fecal egg count reduction tests may

indicate the development of resistance to the dewormer administered. Your parasite management plan should be adjusted accordingly based on regular monitoring.

Environmental Safety

Studies indicate that when eprinomectin comes in contact with soil, it readily and tightly binds to the soil and becomes inactive over time. Free eprinomectin may adversely affect fish and certain aquatic organisms. Do not permit cattle to enter lakes, streams or ponds for at least 6 hours after treatment. Do not contaminate water by direct application or by the improper disposal of drug containers. Dispose of containers in an approved landfill or by incineration.

As with other avermectins, eprinomectin is excreted in the dung of treated animals and can inhibit the reproduction and growth of pest and beneficial insects that use dung as a source of food and for reproduction. The magnitude and duration of such effects are species and life-cycle specific. When used according to label directions, the product is not expected to have an adverse impact on populations of dung-dependent insects.

ADVERSE REACTIONS

No adverse reactions were observed during clinical trials.

STORAGE CONDITIONS

Store bottle or pack in the carton to protect from light and at temperatures up to 86°F/30°C. Storage at temperatures up to 104°F/40°C is permitted for a short period of time, however, such exposure should be minimized.

For the 250 mL or 1 L bottle with a measure-squeeze-pour system, the Metering Cup should not remain attached to the container when not in use. Detach the Metering Cup after each use and replace the shipping cap to close the container top.

HOW SUPPLIED

EPRINEX (eprinomectin) Pour-On for Beef and Dairy Cattle is available in a 250 mL or 1 L bottle with a measure-squeeze-pour system, or in a 2.5 L, 5 L, or 10 L collapsible pack or 20 L container intended for use with appropriate automatic dosing equipment.

Marketed by: Boehringer Ingelheim Animal Health USA Inc.
Duluth, GA 30096

EPRINEX® is a registered trademark of Boehringer Ingelheim Animal Health USA Inc.

©2023 Boehringer Ingelheim Animal Health USA Inc. All rights reserved.

1050-2355-11

Rev. 11-2023